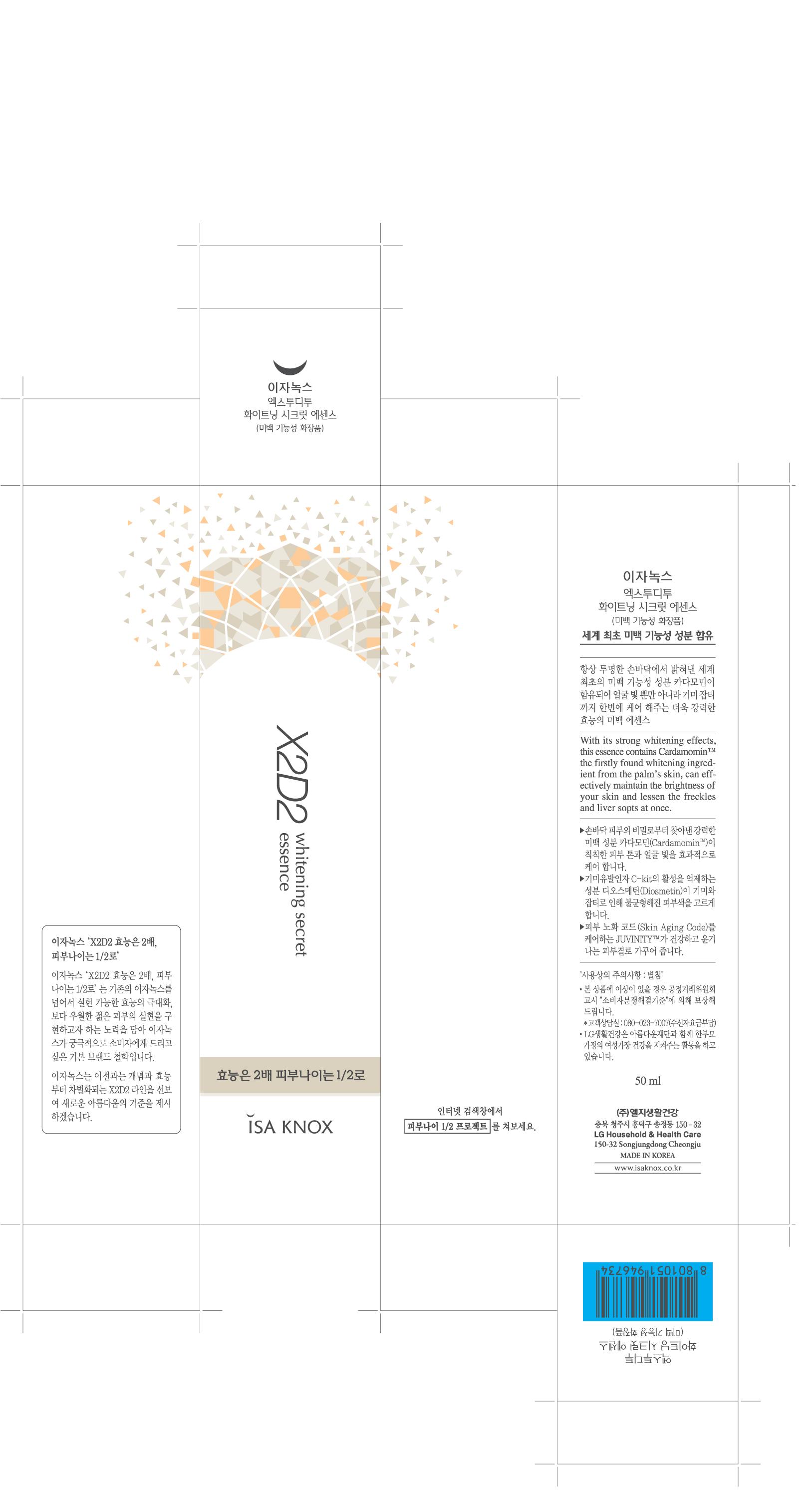 DRUG LABEL: ISAKNOX X202 WHITENING SECRET ESSENCE
NDC: 53208-531 | Form: CREAM
Manufacturer: LG Household and Healthcare, Inc.
Category: otc | Type: HUMAN OTC DRUG LABEL
Date: 20110525

ACTIVE INGREDIENTS: DIOSMETIN 0.055 mL/100 mL
INACTIVE INGREDIENTS: WATER; DIPROPYLENE GLYCOL; TRIETHYLHEXANOIN; GLYCERIN; DOCOSANOL; POLYETHYLENE GLYCOL 400; CETOSTEARYL ALCOHOL; CYCLOMETHICONE 5; ALCOHOL; PONCIRUS TRIFOLIATA FRUIT; ETHYLPARABEN; EDETATE TRISODIUM; NIACINAMIDE; PAEONIA LACTIFLORA ROOT; CANNA INDICA ROOT

Drug Facts

ACTIVE INGREDIENT

DIHYDROXYMETHOXYCHALCON 0.065

DIOSMETIN 0.055%

WARNINGS

For external use only.

Keep out of reach of children. Is swallowed, get medical help or contact a Poison Control Center right away.

PURPOSE

Whitening functional cosmetic.

WHEN USING

Keep out of eyes. Rinse with water to remove.

INDICATIONS AND USAGE

After applying toner, dispense 2-3 amounts and apply gently evenly onto your cheeks, chin, nose, and forehead.

INACTIVE INGREDIENT

WATER, DIPROPYLENE GLYCOL, TRIETHYLHEXANOIN, GLYCERIN, DOCOSANOL, POLYETHYLENE GLYCOL 400, CETOSTEARYL ALCOHOL, CYCLOMETHICONE 5, ALCOHOL, PONCIRUS TRIFOLIATA FRUIT, BETAINE, DIMETHICONE, METHYLPARABEN, TROMETHAMINE, GLYCERYL MONOSTEARATE, PROPYLPARABEN, ETHYLPARABEN, EDETATE TRISODIUM, NIACINAMIDE, PAEONIA LACTIFLORA ROOT, CANNA INDICA ROOT.

DOSAGE AND ADMINISTRATION

The Secret-Kit tm capsules, comprising active whitening ingredients and fine whine particles, will burst as the essence gets absorbed, transforming your dull, lifeless complexion into more pure and transparent skin.